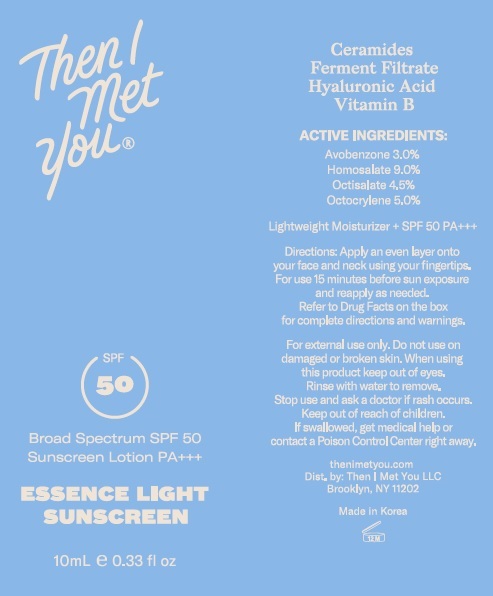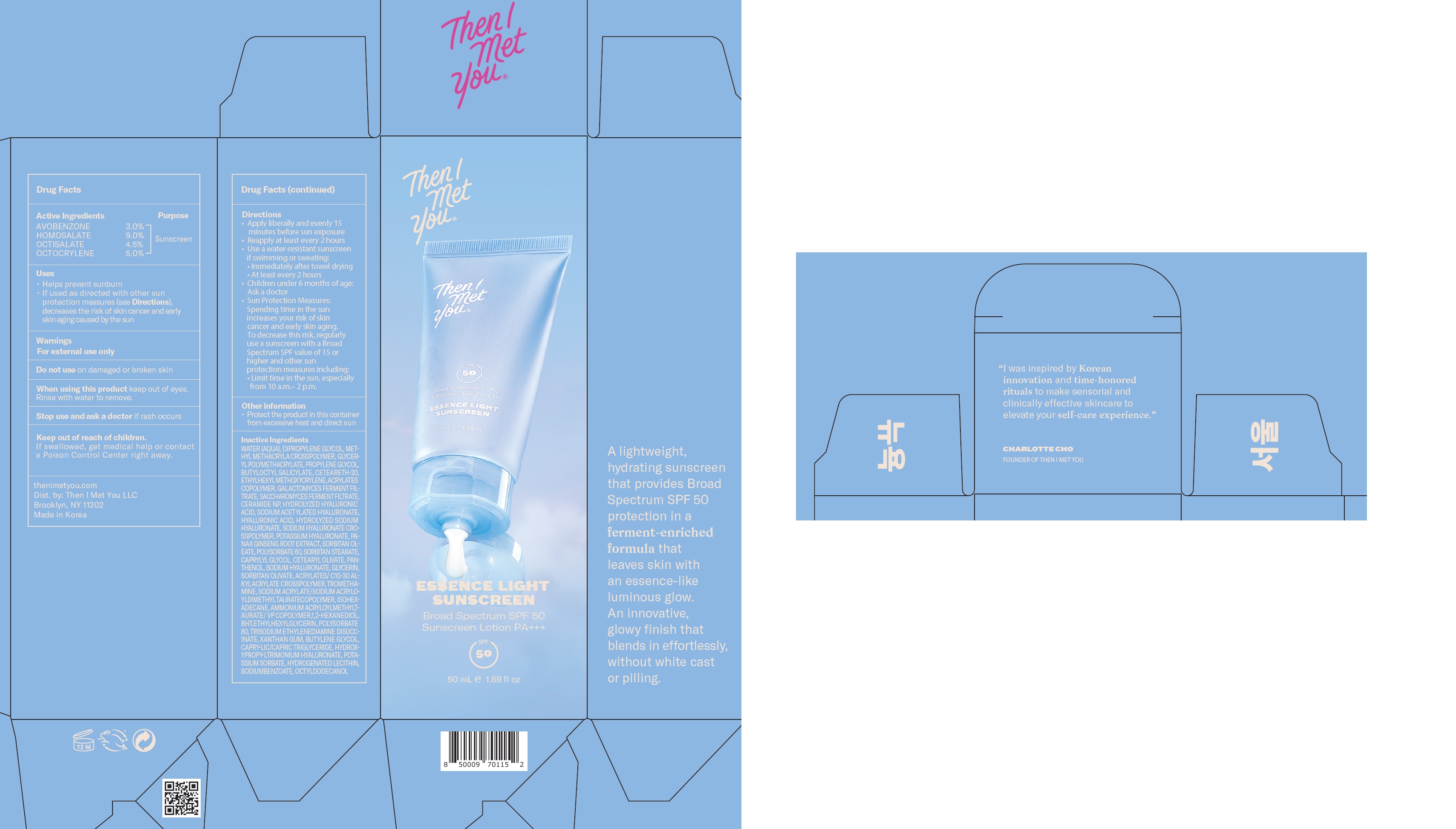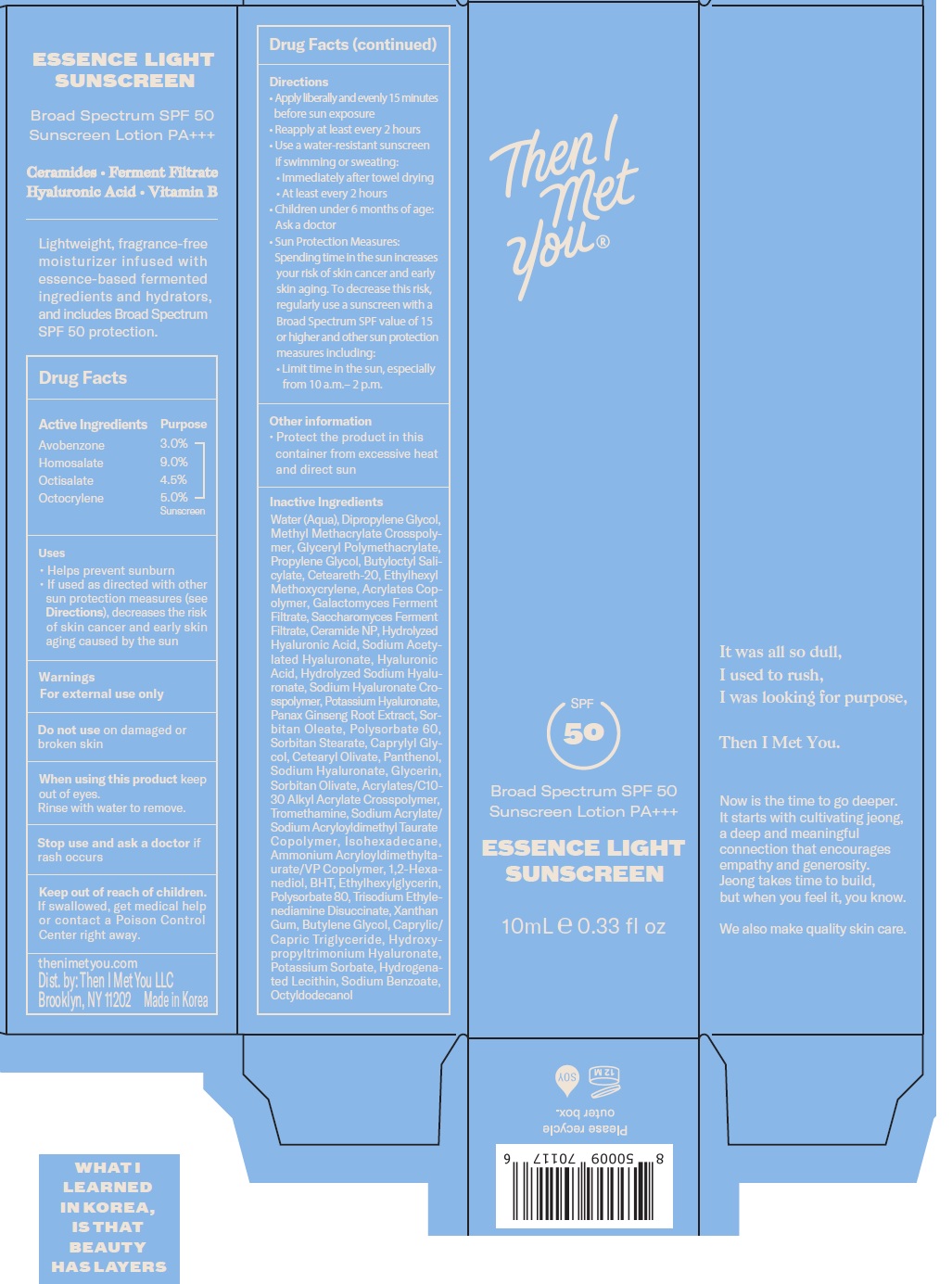 DRUG LABEL: ESSENCE LIGHT SUNSCREEN SPF 50 PA
NDC: 14268-119 | Form: LOTION
Manufacturer: ENGLEWOOD LAB, INC.
Category: otc | Type: HUMAN OTC DRUG LABEL
Date: 20250131

ACTIVE INGREDIENTS: AVOBENZONE 30 mg/1 mL; HOMOSALATE 90 mg/1 mL; OCTISALATE 45 mg/1 mL; OCTOCRYLENE 50 mg/1 mL
INACTIVE INGREDIENTS: WATER; DIPROPYLENE GLYCOL; PROPYLENE GLYCOL; BUTYLOCTYL SALICYLATE; POLYOXYL 20 CETOSTEARYL ETHER; ETHYLHEXYL METHOXYCRYLENE; CERAMIDE NP; SODIUM ACETYLATED HYALURONATE; HYALURONIC ACID; ASIAN GINSENG; SORBITAN MONOOLEATE; POLYSORBATE 60; SORBITAN MONOSTEARATE; CAPRYLYL GLYCOL; CETEARYL OLIVATE; PANTHENOL; HYALURONATE SODIUM; GLYCERIN; SORBITAN OLIVATE; TROMETHAMINE; ISOHEXADECANE; 1,2-HEXANEDIOL; BUTYLATED HYDROXYTOLUENE; ETHYLHEXYLGLYCERIN; POLYSORBATE 80; TRISODIUM ETHYLENEDIAMINE DISUCCINATE; XANTHAN GUM; BUTYLENE GLYCOL; MEDIUM-CHAIN TRIGLYCERIDES; POTASSIUM SORBATE; SODIUM BENZOATE; OCTYLDODECANOL

ESSENCE LIGHT SUNSCREEN SPF 50 PA +++

Active Ingredients

AVOBENZONE 3.0%
HOMOSALATE 9.0%
OCTISALATE 4.5%
OCTOCRYLENE 5.0%

Purpose

Sunscreen

Uses

- Helps prevent sunburn
- if used as directed with other sun protection measures (see Directions), decreases the risk of skin cancer and early skin aging caused by the sun.

Warnings

- For external use only.

Do not use

on damaged or broken skin

When using this product

keep out of eyes. Rinse with water to remove.

Stop use and ask a doctor if

rash occurs.

Keep out of reach of children.

If swallowed, get medical help or contact a Poison Control Center right away.

Directions

- Apply liberally and evenly 15 minutes before sun exposure
- Reapply at least every 2 hours
- Use a water-resistant sunscreen if swimming or sweating:
- Immediately after towel drying
- At least every 2 hours
- Children under 6 months of age: Ask a doctor
- Sun Protection Measures: Spending time in the sun increases your risk of skin cancer and early skin aging. To decrease this risk, regularly use a sunscreen with a Broad Spectrum SPF value of 15 or higher and other sun protection measures including:
- Limit time in the sun, especially from 10 a.m.– 2 p.m.

Other information

• Protect the product in this container from excessive heat and direct sun

Inactive Ingredients

WATER (AQUA), DIPROPYLENE GLYCOL, METHYL METHACRYLA CROSSPOLYMER, GLYCERYL POLYMETHACRYLATE, PROPYLENE GLYCOL, BUTYLOCTYL SALICYLATE, CETEARETH-20, ETHYLHEXYL METHOXYCRYLENE, ACRYLATES COPOLYMER, GALACTOMYCES FERMENT FILTRATE, SACCHAROMYCES FERMENT FILTRATE, CERAMIDE NP, HYDROLYZED HYALURONIC ACID, SODIUM ACETYLATED HYALURONATE, HYALURONIC ACID, HYDROLYZED SODIUM HYALURONATE, SODIUM HYALURONATE CROSSPOLYMER, POTASSIUM HYALURONATE, PANAX GINSENG ROOT EXTRACT, SORBITAN OLEATE, POLYSORBATE 60, SORBITAN STEARATE, CAPRYLYL GLYCOL, CETEARYL OLIVATE, PANTHENOL, SODIUM HYALURONATE, GLYCERIN, SORBITAN OLIVATE, ACRYLATES/ C10-30 ALKYL ACRYLATE CROSSPOLYMER, TROMETHAMINE, SODIUM ACRYLATE/ SODIUM ACRYLOYLDIMETHYL TAURATECOPOLYMER, ISOHEXADECANE, AMMONIUM ACRYLOYLMETHYLTAURATE/ VP COPOLYMER, 1,2-HEXANEDIOL,BHT,ETHYLHEXYLGLYCERIN, POLYSORBATE 80, TRISODIUM ETHYLENEDIAMINE DISUCCINATE, XANTHAN GUM, BUTYLENE GLYCOL, CAPRYLIC/CAPRIC TRIGLYCERIDE, HYDROXYPROPY-LTRIMONIUM HYALURONATE, POTASSIUM SORBATE, HYDROGENATED LECITHIN, SODIUMBENZOATE, OCTYLDODECANOL